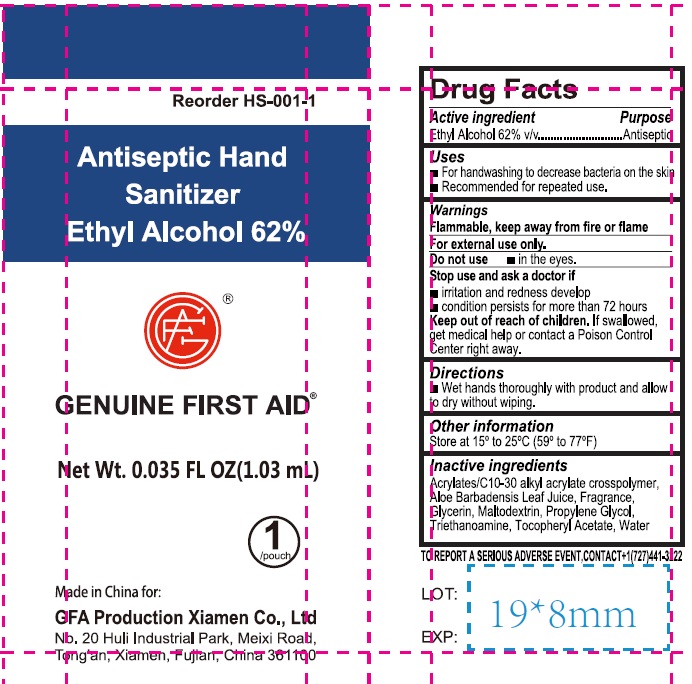 DRUG LABEL: GENUINE FIRST AID Antiseptic Hand Sanitizer
NDC: 43473-013 | Form: GEL
Manufacturer: Nantong Health & Beyond Hygienic Products Inc.
Category: otc | Type: HUMAN OTC DRUG LABEL
Date: 20231019

ACTIVE INGREDIENTS: ALCOHOL 62 mL/100 mL
INACTIVE INGREDIENTS: WATER; GLYCERIN; PROPYLENE GLYCOL; ACRYLATES/C10-30 ALKYL ACRYLATE CROSSPOLYMER (60000 MPA.S); TOCOPHERYL GLUCOSIDE; TRICLOSAN; MALTODEXTRIN; ALOE

43473-013 Genuine First Aid Hand Sanitizer

Active ingredient

Ethyl Alcohol, 62% v/v

Purpose Antiseptic

Uses

For hand washing to decrease bacteria on the skin

Recommended for repeated use

Warnings

For external use only.

Flammable, keep away from fire or flame.

Do not usein the eyes

Stop use and ask a doctor if

- irritation and redness develop
- condition persists for more than 72 hours

Keep out of reach of children. If swallowed, get medical help or contact a Poison Control Center right away.

Directions

Wet hands throughly with product and allow to dry withour wiping

Other information

Store at 15C to 25C (59F to 77F)

Inactive ingredients

Acrylates/ C10-C30 alkyl acrylate crossploymer, Aloe barbadensis leaf jiuce, Fragrance, Glycerin, Maltodextrin, Propylene glycol, Triethanolamine, Tocopheryl acetate, Water